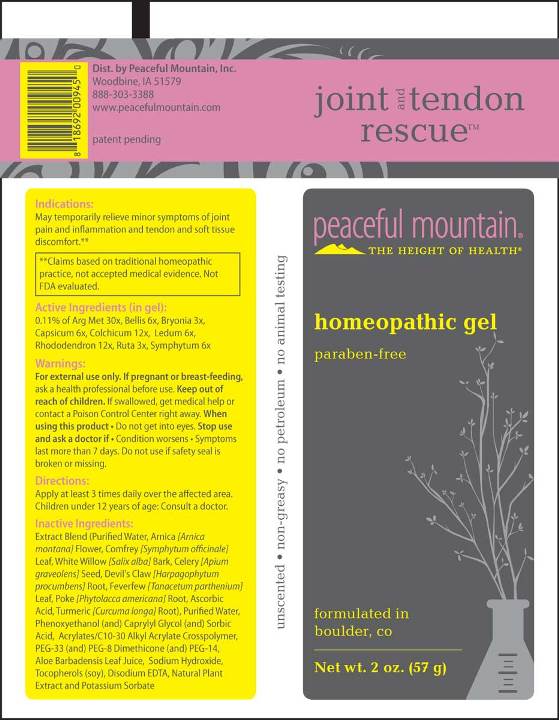 DRUG LABEL: Joint and Tendon Rescue
NDC: 43846-0077 | Form: GEL
Manufacturer: Peaceful Mountain, Inc.
Category: homeopathic | Type: HUMAN OTC DRUG LABEL
Date: 20181212

ACTIVE INGREDIENTS: BRYONIA ALBA ROOT 3 [hp_X]/1 g; RUTA GRAVEOLENS FLOWERING TOP 3 [hp_X]/1 g; BELLIS PERENNIS 6 [hp_X]/1 g; CAPSICUM 6 [hp_X]/1 g; LEDUM PALUSTRE TWIG 6 [hp_X]/1 g; COMFREY ROOT 6 [hp_X]/1 g; WHEY 12 [hp_X]/1 g; COLCHICUM AUTUMNALE BULB 12 [hp_X]/1 g; RHODODENDRON AUREUM LEAF 30 [hp_X]/1 g
INACTIVE INGREDIENTS: WATER; PHENOXYETHANOL; CAPRYLYL GLYCOL; SORBIC ACID; SODIUM HYDROXIDE; CARBOMER INTERPOLYMER TYPE A (ALLYL SUCROSE CROSSLINKED); POLYETHYLENE GLYCOL 1500; PEG-8 DIMETHICONE; POLYETHYLENE GLYCOL 700; ALOE VERA LEAF; TOCOPHEROL; EDETATE DISODIUM; OREGANO; POTASSIUM SORBATE; ARNICA MONTANA FLOWER; COMFREY LEAF; SALIX ALBA BARK; CELERY SEED; HARPAGOPHYTUM PROCUMBENS ROOT; FEVERFEW; PHYTOLACCA AMERICANA ROOT; ASCORBIC ACID; TURMERIC

Drug Facts:

ACTIVE INGREDIENTS:

(in gel): 0.11% of Argentum Metallicum 30X, Bellis Perennis 6X, Bryonia (Alba) 3X, Capsicum Annuum 6X, Colchicum Autumnale 12X, Ledum Palustre 6X, Rhododendron Chrysanthum 12X, Ruta Graveolens 3X, Symphytum Officinale 6X

INDICATIONS:

May temporarily relieve minor symptoms of joint pain and inflammation and tendon and soft tissue discomfort.**

**Claims based on traditional homeopathic practice, not accepted medical evidence. Not FDA evaluated.

WARNINGS:

For external use only.

If pregnant or breast-feeding, ask a health professional before use.

Keep out of reach of children. If swallowed, get medical help or contact a Poison Control Center right away.

When using this product • Do not get into eyes.

Stop use and ask a doctor if • Conditions worsens • Symptoms last more than 7 days

Do not use if safety seal is broken or missing.

Keep out of reach of children. If swallowed, get medical help or contact a Poison Control Center right away.

DIRECTIONS:

Apply at least 3 times daily over the affected area.

Children under 12 years of age: Consult a doctor.

INDICATIONS:

May temporarily relieve minor symptoms of joint pain and inflammation and tendon and soft tissue discomfort.**

**Claims based on traditional homeopathic practice, not accepted medical evidence. Not FDA evaluated.

INACTIVE INGREDIENTS:

Purified Water, Phenoxyethanol (and) Caprylyl Glycol (and) Sorbic Acid, Sodium Hydroxide (Solution), Acrylates/C10-30 Alkyl Acrylate Crosspolymer (Carbopol (Ultrez 21), PEG-33 (and) PEG-8 Dimethicone (and) PEG-14, Aloe Barbadensis Leaf Juice (Aloe Vera 10X Concentrate), Tocopherols [Vitamin E Oil] (derived from Soy Bean), Edetate Disodium (EDTA), Potassium Sorbate, Arnica (flower), Comfrey (leaf), White Willow (bark), Celery (seed), Devil’s Claw (root), Feverfew (leaf), Poke (root), Ascorbic Acid, Turmeric (Root).

QUESTIONS:

Dist. by Peaceful Mountain, Inc.
Woodbine, IA 51579

888-303-3388
www.peacefulmountain.com

PACKAGE LABEL DISPLAY:

joint and tendon rescue
peaceful mountain
THE HEIGHT OF HEALTH
homeopathic gel
paraben-free
formulated in
boulder, co
Net wt. 2 oz. (57 g)